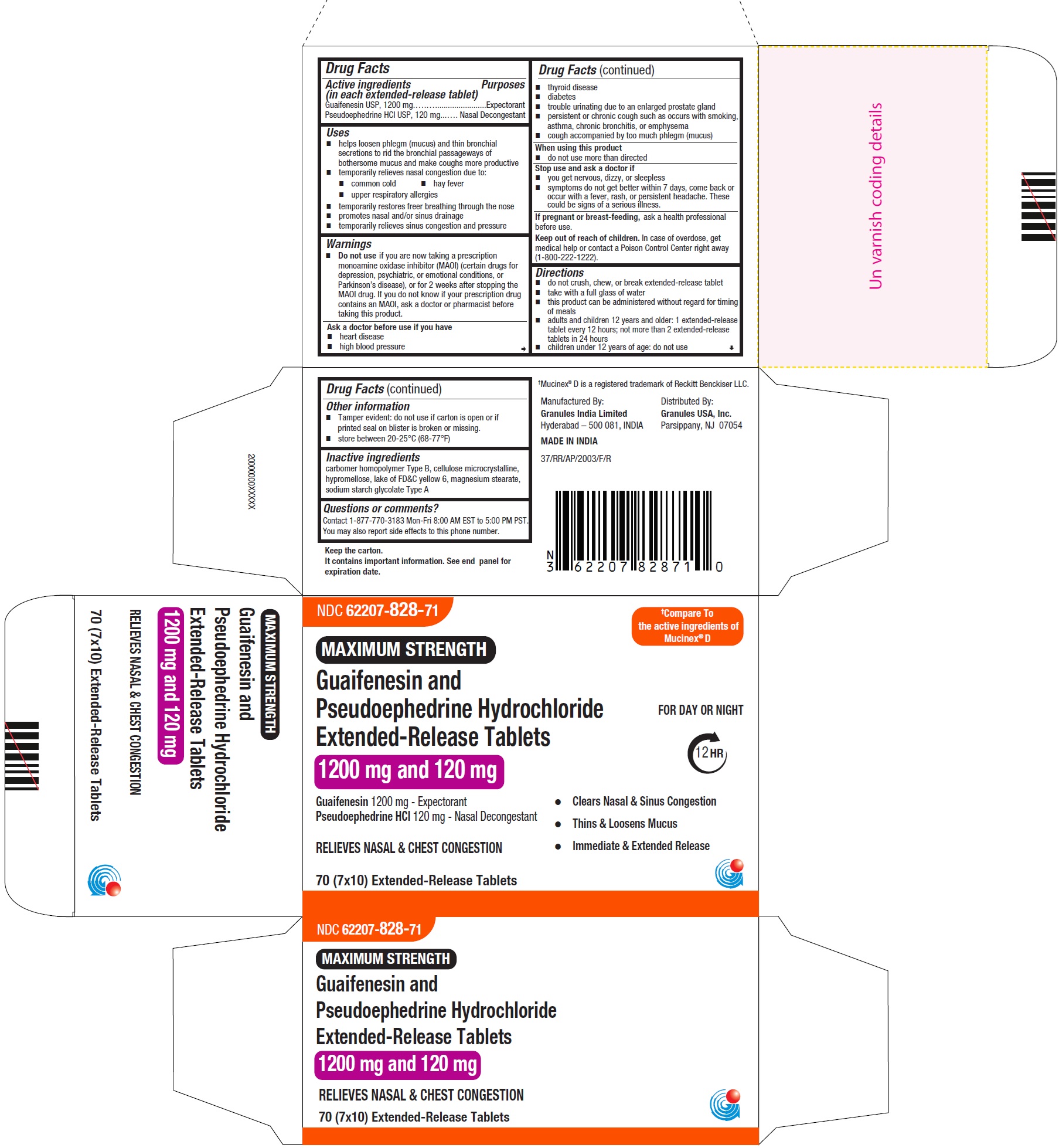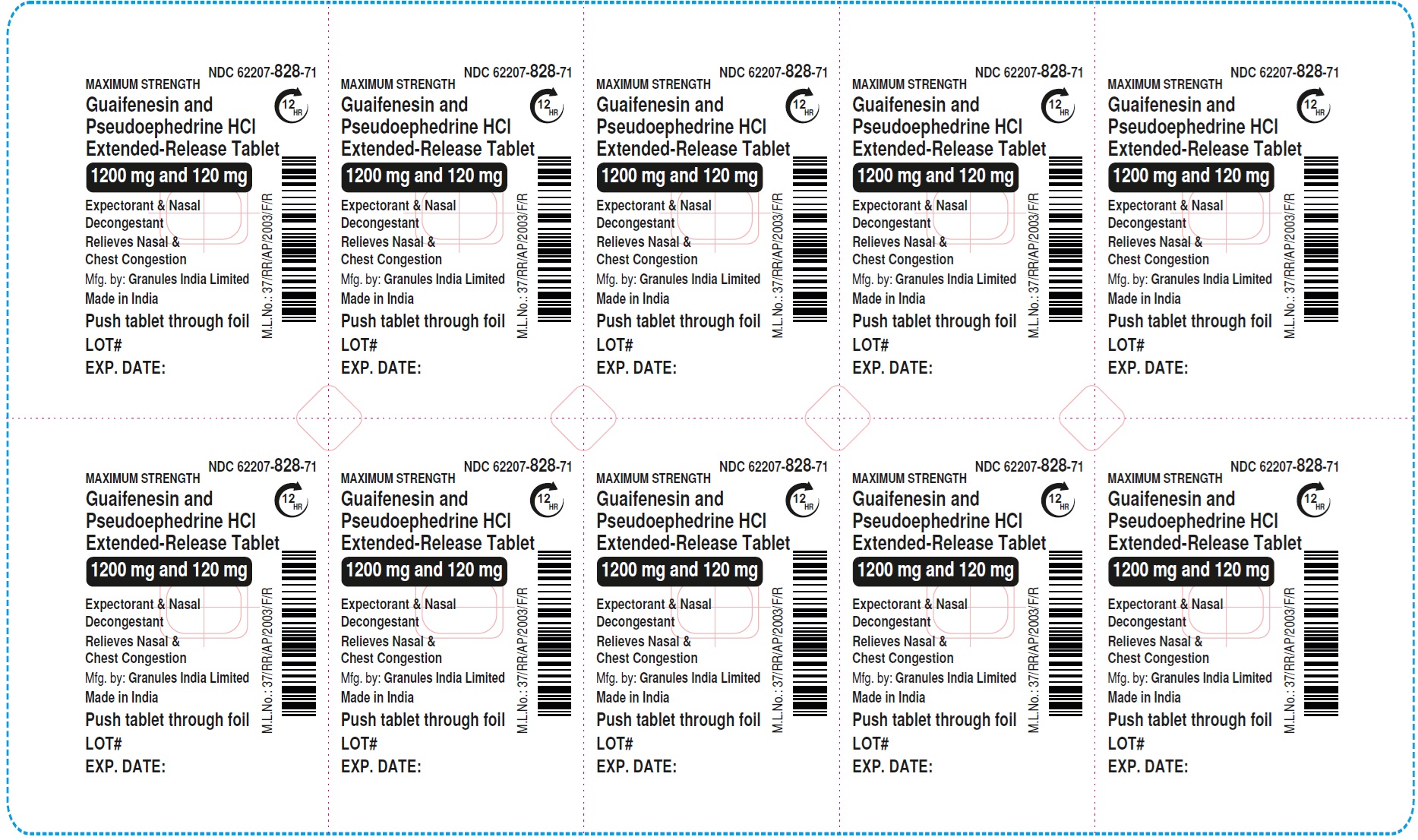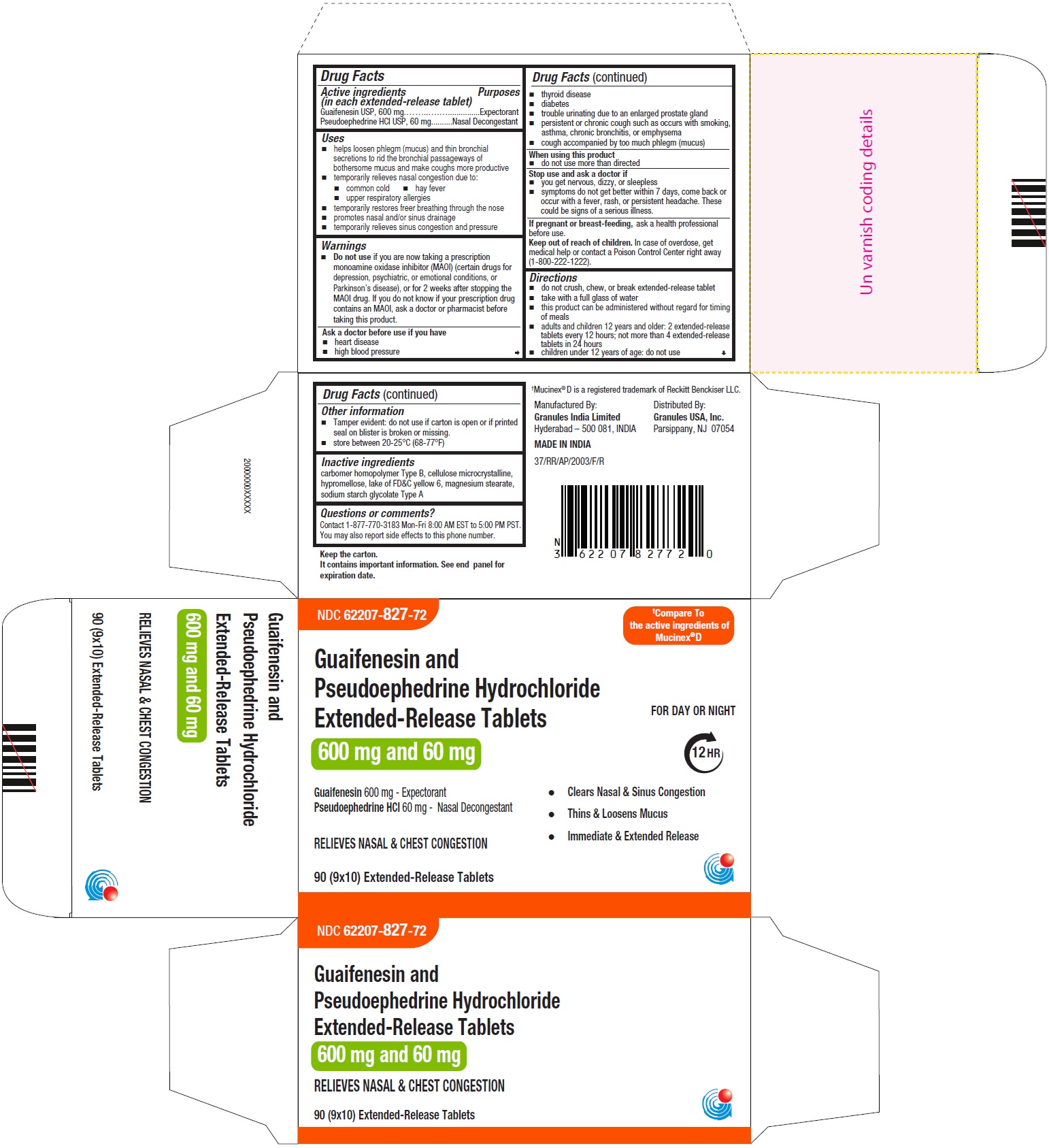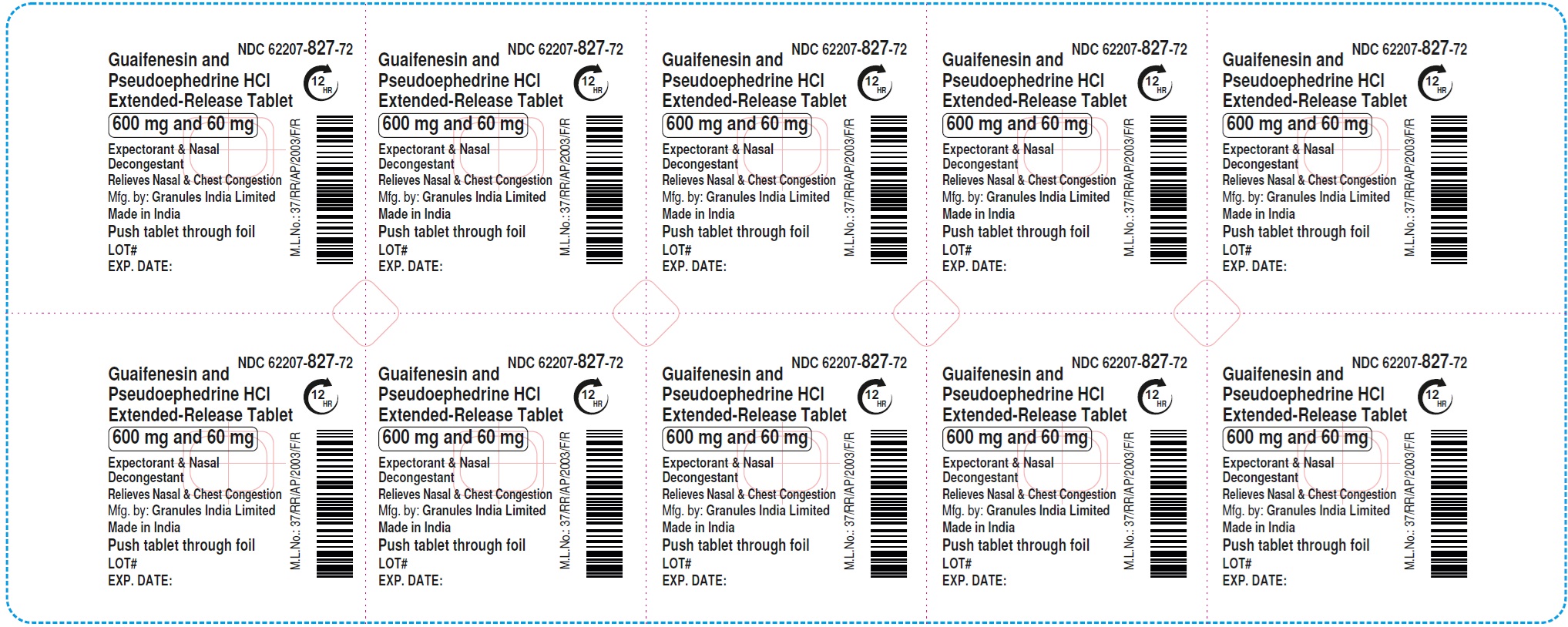 DRUG LABEL: Guaifenesin and Pseudoephedrine HCl
NDC: 62207-827 | Form: TABLET, EXTENDED RELEASE
Manufacturer: Granules India Ltd
Category: otc | Type: HUMAN OTC DRUG LABEL
Date: 20251202

ACTIVE INGREDIENTS: GUAIFENESIN 600 mg/1 1; PSEUDOEPHEDRINE HYDROCHLORIDE 60 mg/1 1
INACTIVE INGREDIENTS: MAGNESIUM STEARATE; FD&C YELLOW NO. 6; CARBOMER HOMOPOLYMER TYPE B (ALLYL PENTAERYTHRITOL CROSSLINKED); CELLULOSE, MICROCRYSTALLINE; SODIUM STARCH GLYCOLATE TYPE A; HYPROMELLOSE 2910 (5 MPA.S); HYPROMELLOSE 2910 (10000 MPA.S)

Guaifenesin and Pseudoephedrine HCl Extended-Release Tablets, 600 mg/60 mg and 1200 mg/120 mg
Drug Facts

Active ingredients (in each extended-release tablet)

(For 600 mg/60 mg)

Guaifenesin USP, 600 mg

Pseudoephedrine HCL USP, 60 mg
(For 1200 mg/120 mg)

Guaifenesin USP, 1200 mg
Pseudoephedrine HCL USP, 120 mg

Purposes

Expectorant
Nasal Decongestant

Uses

• helps loosen phlegm (mucus) and thin bronchial secretions to rid the bronchial passageways of bothersome mucus and make coughs more productive
• temporarily relieves nasal congestion due to:
• common cold
• hay fever
• upper respiratory allergies
• temporarily restores freer breathing through the nose
• promotes nasal and/or sinus drainage
• temporarily relieves sinus congestion and pressure

Warnings

 Do not use if you are now taking a prescription monoamine oxidase inhibitor (MAOI) (certain drugs for depression, psychiatric, or emotional conditions, or Parkinson’s disease), or for 2 weeks after stopping the MAOI drug. If you do not know if your prescription drug contains an MAOI, ask a doctor or pharmacist before taking this product.

Ask a doctor before use if you have

• heart disease
• high blood pressure
• thyroid disease
• diabetes
• trouble urinating due to an enlarged prostate gland
• persistent or chronic cough such as occurs with smoking, asthma, chronic bronchitis, or emphysema
• cough accompanied by too much phlegm (mucus)

When using this product

• do not use more than directed

Stop use and ask a doctor if

• you get nervous, dizzy, or sleepless
• symptoms do not get better within 7 days, come back or occur with a fever, rash, or persistent headache. These could be signs of a serious illness.

PREGNANCY OR BREAST FEEDING

If pregnant or breast-feeding, ask a health professional before use.

Keep out of reach of children. In case of overdose, get medical help or contact a Poison Control Centre right away (1-800 222-1222).

Directions

• do not crush, chew, or break extended-release tablet
• take with a full glass of water
• this product can be administered without regard for timing of meals
• adults and children 12 years and older:
For 600 mg/60 mg: 2 extended-release tablets every 12 hours; not more than 4 extended-release tablets in 24 hours
For 1200 mg/120 mg: 1 extended-release tablet every 12 hours; not more than 2 extended-release tablets in 24 hours
• children under 12 years of age: do not use

Other information

• Tamper evident: do not use if carton is open or if printed seal on blister is broken or missing.
• store between 20-25°C (68-77°F)

Inactive ingredients

carbomer homopolymer Type B, cellulose microcrystalline, hypromellose, lake of FD&C yellow 6, magnesium stearate, sodium starch glycolate Type A

Questions or comments?

Contact 1-877-770-3183 Mon-Fri 8:00 AM EST to 5:00 PM PST.
You may also report side effects to this phone number.
Keep the carton.
It contains important information. See end panel for expiration date.
Manufactured By:
Granules India Limited
Hyderabad – 500 081, INDIA
MADE IN INDIA

Distributed By:
Granules USA, Inc.
Parsippany, NJ 07054

PRINCIPAL DISPLAY PANEL 600 mg and 60 mg - Blister Carton Label

NDC 62207-827-72†Compare To
the active ingredients of
Mucinex® D

Guaifenesin and
Pseudoephedrine Hydrochloride FOR DAY OR NIGHT

Extended-Release Tablets 12HR

600 mg and 60 mg

Guaifenesin 600 mg - Expectorant • Clears Nasal & Sinus Congestion
Pseudoephedrine HCl 60 mg - Nasal Decongestant • Thins & Loosens Mucus
• Immediate & Extended Release

RELIEVES NASAL & CHEST CONGESTION

90 (9x10) Extended-Release Tablets

PRINCIPAL DISPLAY PANEL 1200 mg and 120 mg - Blister Carton Label

NDC 62207-828-71†Compare To
the active ingredients of
Mucinex® D

Guaifenesin and
Pseudoephedrine Hydrochloride FOR DAY OR NIGHT
Extended-Release Tablets 12HR

1200 mg and 120 mg

Guaifenesin 1200 mg - Expectorant • Clears Nasal & Sinus Congestion
Pseudoephedrine HCl 120 mg - Nasal Decongestant • Thins & Loosens Mucus
• Immediate & Extended Release

RELIEVES NASAL & CHEST CONGESTION

70 (7x10) Extended-Release Tablets